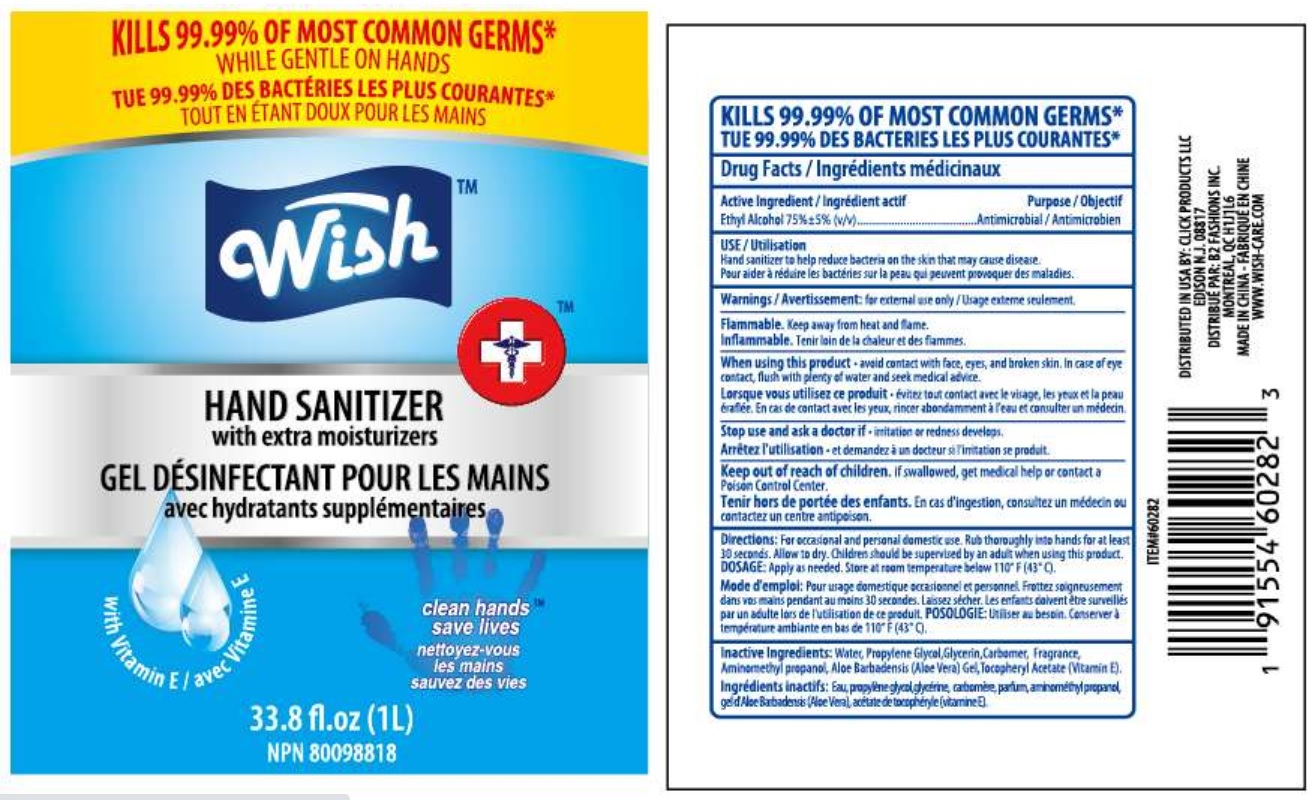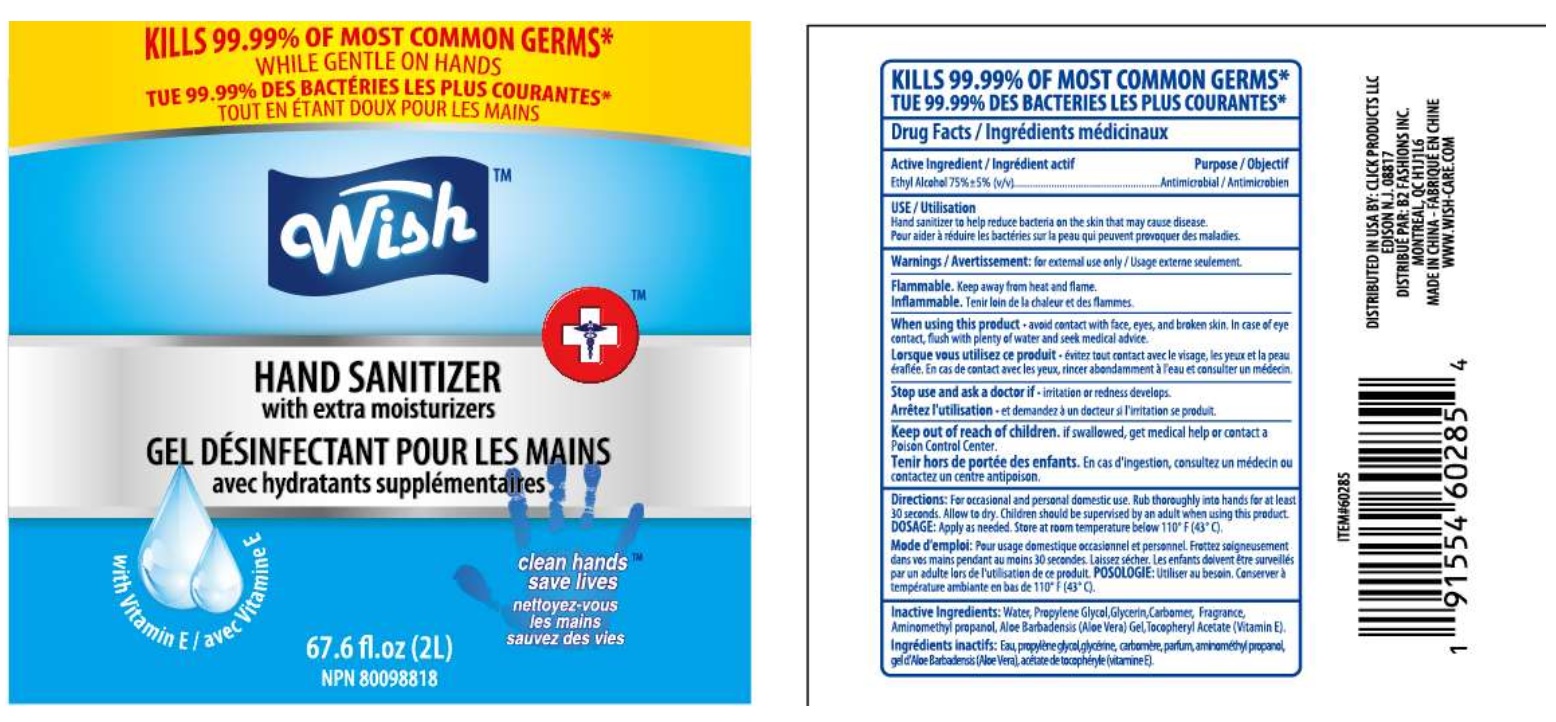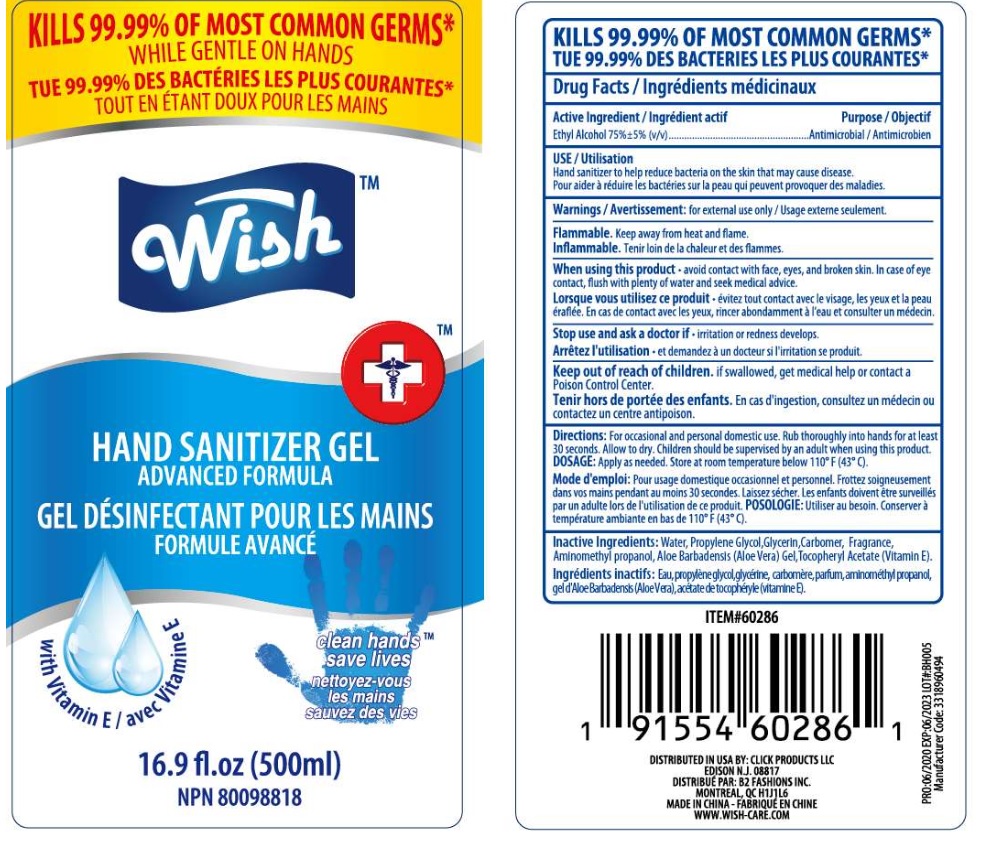 DRUG LABEL: Wish hand sanitizer
NDC: 71611-041 | Form: GEL
Manufacturer: Click Products LLC
Category: otc | Type: HUMAN OTC DRUG LABEL
Date: 20200617

ACTIVE INGREDIENTS: ALCOHOL 75 mL/100 mL
INACTIVE INGREDIENTS: CARBOMER 940 0.3 mL/100 mL; GLYCERIN 0.5 mL/100 mL; PROPYLENE GLYCOL 0.5 mL/100 mL; AMINOMETHYLPROPANOL 0.14 mL/100 mL; .ALPHA.-TOCOPHEROL ACETATE 0.05 mL/100 mL; ALOE VERA LEAF 0.05 mL/100 mL; WATER 27.86 mL/100 mL

Hand sanitizer -Wish Advanced

DESCRIPTION

KILLS 99.99% OF MOST COMMON GERMS

Drug facts

Active Ingredient Purpose

Ethyl Alcohol 75%±5% v/v ....Antimicrobial

USE

Hand sanitizer to help reduce bacteria on the skin that may cause disease.

Warning

For external use only.

Flammable, Keep away from heat and flame.

WHEN USING THIS PRODUCT

Avoid contact with face, eyes and broken skin. In case of eye contact, flush with plenty of water and seek medical advice.

Stop use and ask a doctor if irritation or redness develops.

Keep out of reach of children.

If swallowed get immediate medical help or contact a poison control center.

Direction:

For occasional and personal domestic use. Rub thoroughly into hands for at least 30 seconds. Allow to dry. Children should be supervised by an adult when using this product.

Dosage

Apply as needed. Store at room temperature below 110oF (43oC).

Inactive Ingredients:

Water(aqua), Propylene Glycol, Glycerin, Carbomer, Fragrance, Aminomethyl Propanol, Aloe Barbadensis(Aloe Vera) Gel, Tocopheryl acetate(vitamin E).